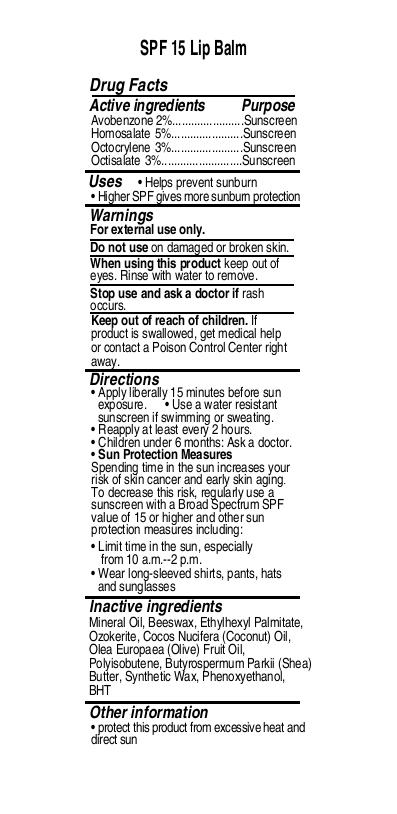 DRUG LABEL: natural lip balm SPF15(unflavored)
NDC: 82953-029 | Form: LIPSTICK
Manufacturer: Cosmuses Cosmetics (Ningbo) Co., Ltd.
Category: otc | Type: HUMAN OTC DRUG LABEL
Date: 20250123

ACTIVE INGREDIENTS: OCTOCRYLENE 3 g/100 g; HOMOSALATE 5 g/100 g; AVOBENZONE 2 g/100 g; OCTISALATE 3 g/100 g
INACTIVE INGREDIENTS: BUTYROSPERMUM PARKII (SHEA) BUTTER; BHT; MINERAL OIL; BEESWAX; ETHYLHEXYL PALMITATE; CERESIN; PHENOXYETHANOL; SYNTHETIC WAX (1800 MW); POLYISOBUTYLENE (1000 MW); COCOS NUCIFERA (COCONUT) OIL; OLEA EUROPAEA FRUIT VOLATILE OIL

SPF15 natural lip balm (no flavor)

Drug Facts

Active ingredients

Avobenzone 2%

Homosalate 5%

Octocrylene 3%

Octisalate 3%

Purpose

Sunscreen

Uses

- Helps prevent sunburn
- Higher SPF giwes more sunburn protection

Warnings

For external use only

WARNINGS

For external use only

Do not use on damaged or broken skin.

When using this product keep out of eyes. Rinse with water to remove.

Stop use and ask a doctor if rash occurs.

Keep out of reach of children. If product is swallowed, get medical help or contact a Poison Control Center right away.

Directions

- Apply liberally 15minutes before sun exposure
- Use a water resistant sunscreen if swimming or sweating.
- Reapply at least every 2 hours.
- Children under 6 months of age: ask a doctor.
- Sun Protection Measures

Spending time in the sun increases your risk of skin cancer and early skin aging.

To decreases this risk, regularly use a sunscreen with a Broad Spectrum SPF value of 15 or higher and other sun protection measures including:

- limit time in the sun, especially from 10a.m.- 2p.m.
- wear long-sleeve shirts, pants, hats and sunglasses

Inactive ingredients

Mineral Oil, Beeswax, Ethylhexyl Palmitate, Ozokerite, Cocos Nucifera (Coconut) Oil,Olea Europaea (Olive) Fruit Oil,Polyisobutene, Butyrospermum Parkii (Shea) Butter, Synthetic Wax, Phenoxyethanol, BHT

Other information

Protect this product from excessive heat and direct sun